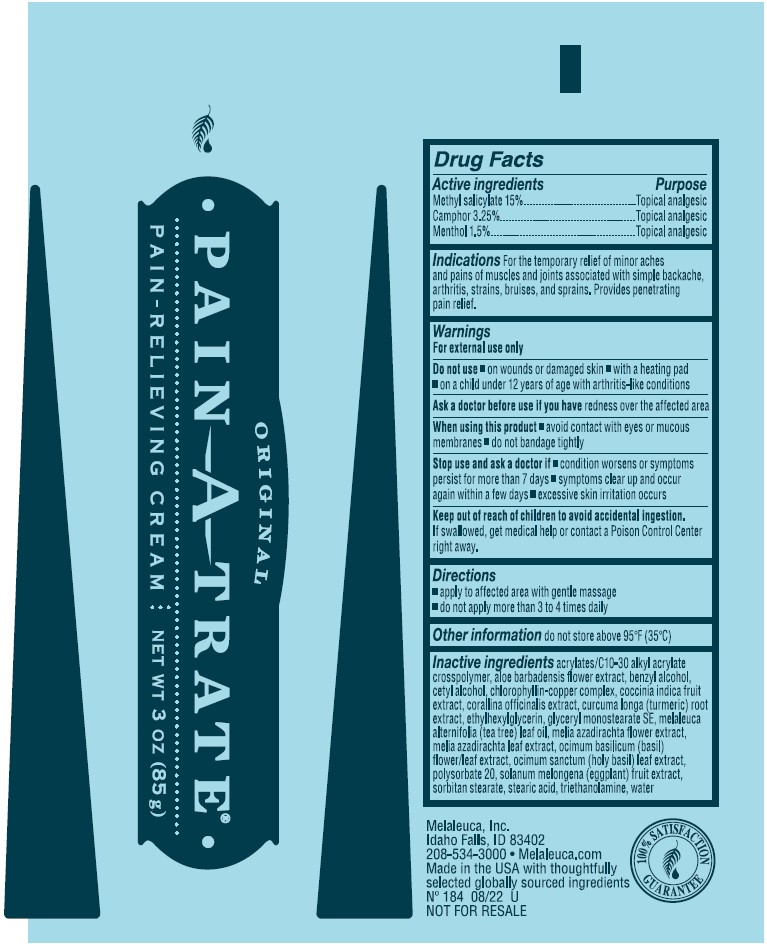 DRUG LABEL: Original Pain-A-Trate
NDC: 54473-335 | Form: CREAM
Manufacturer: Melaleuca, Inc.
Category: otc | Type: HUMAN OTC DRUG LABEL
Date: 20251231

ACTIVE INGREDIENTS: CAMPHOR (SYNTHETIC) 32.5 mg/1 g; MENTHOL 15 mg/1 g; METHYL SALICYLATE 150 mg/1 g
INACTIVE INGREDIENTS: AZADIRACHTA INDICA FLOWER; GLYCERYL STEARATE SE; WATER; STEARIC ACID; CETYL ALCOHOL; SORBITAN MONOSTEARATE; POLYSORBATE 20; TEA TREE OIL; COCCINIA GRANDIS FRUIT; ETHYLHEXYLGLYCERIN; BENZYL ALCOHOL; CORALLINA OFFICINALIS; CURCUMA LONGA WHOLE; OCIMUM BASILICUM FLOWERING TOP; OCIMUM GRATISSIMUM LEAF OIL; TROLAMINE; SODIUM COPPER CHLOROPHYLLIN A; AZADIRACHTA INDICA LEAF; SOLANUM MELONGENA WHOLE; ALOE VERA FLOWER; CARBOMER INTERPOLYMER TYPE A (ALLYL SUCROSE CROSSLINKED)

Original Pain-A-Trate Pain-Relieving Cream

Active ingredients
Camphor 3.25%
Menthol, 1.5%
Methyl Salicylate, 15%

Purpose
Topical analgesic

INDICATIONS AND USAGE

Indications For the temporary relief of minor aches and pains of muscles and joints associated with simple backache, arthritis, strains, bruises, sprains. Provides penetrating pain relief.

Warnings
For external use only

Do not use

- on wounds or damaged skin
- with a heating pad
- on a child under 12 years of age with arthritis-like conditions

Ask a doctor before use if you have redness over the affected area.

When using this product

- avoid contact with eyes or mucus membranes
- do not bandage tightly

Stop use and ask a doctor if

- condition worsens or symptoms persist for more than 7 days
- symptoms clear up and occur again within a few days
- excessive skin irritation occurs

Keep out of reach of children to avoid accidental ingestion. If swallowed, get medical help or contact a Poison Control Center right away.

Directions

- apply to affected area with gentle massage
- do not apply more than 3 to 4 times daily

Other information do not store above 95°F (35°C)

INACTIVE INGREDIENT

Inactive ingredients acrylates/C10-30 alkyl acrylate crosspolymer, aloe barbadensis flower extract, benzyl alcohol, cetyl alcohol, chlorophyllin-copper complex, coccinia indica fruit extract, corallina officianalis extract, curcuma longa (turmeric) root extract, ethylhexylglyverin, glyceryl monostearate SE, melaleuca alternifolia (tea tree) leaf oil, melia azadirachta flower extract, melia azadirachta leaf extract, ocimum basilicum (basil) flower/leaf extract, ocimum sanctum (holy basil) leaf extract, polysorbate 20, solanum melongena (eggplant) fruit extract, sorbitan stearate, stearic acid, triethanolamine, water